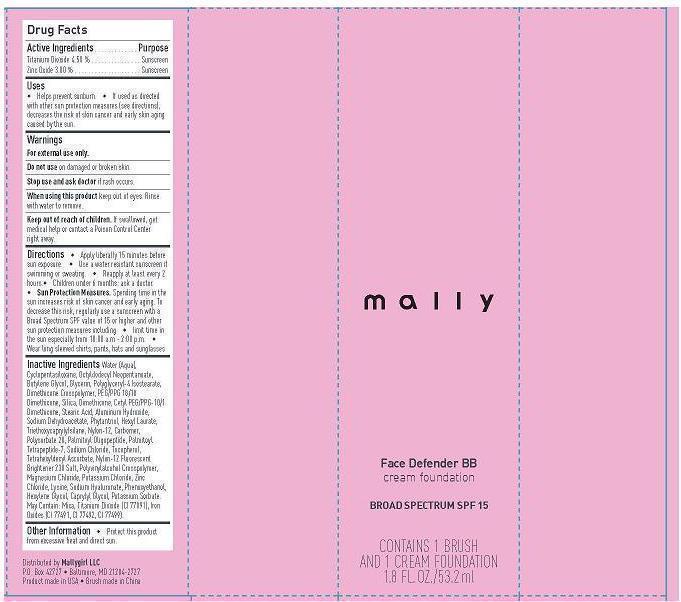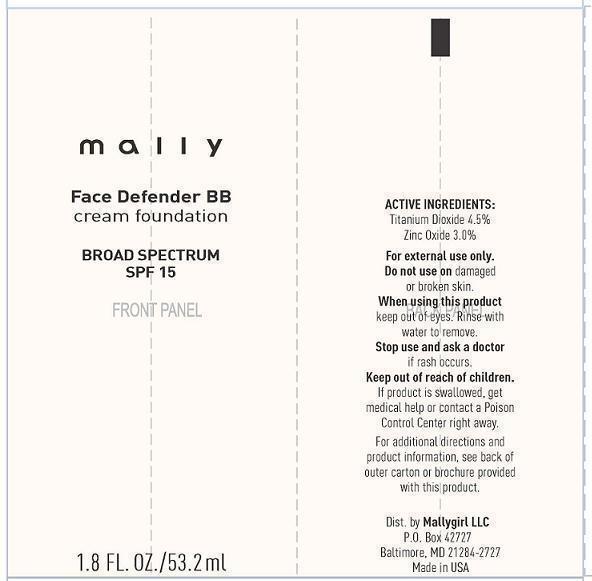 DRUG LABEL: mally Face Defender Foundation BB
NDC: 76119-1445 | Form: CREAM
Manufacturer: MallyGirl, LLC
Category: otc | Type: HUMAN OTC DRUG LABEL
Date: 20140204

ACTIVE INGREDIENTS: TITANIUM DIOXIDE 2.39 mg/53.2 mL; ZINC OXIDE 1.59 mg/53.2 mL
INACTIVE INGREDIENTS: WATER; OCTYLDODECYL NEOPENTANOATE; BUTYLENE GLYCOL; GLYCERIN; POLYGLYCERYL-4 ISOSTEARATE; PEG/PPG-18/18 DIMETHICONE; SILICON DIOXIDE; DIMETHICONE; CETYL PEG/PPG-10/1 DIMETHICONE (HLB 2); STEARIC ACID; ALUMINUM HYDROXIDE; SODIUM DEHYDROACETATE; PHYTANTRIOL; HEXYL LAURATE; TRIETHOXYCAPRYLYLSILANE; NYLON-12; CARBOMER 940; POLYSORBATE 20; PALMITOYL OLIGOPEPTIDE; PALMITOYL TETRAPEPTIDE-7; SODIUM CHLORIDE; TOCOPHEROL; TETRAHEXYLDECYL ASCORBATE; POLYVINYL ALCOHOL; CYCLOMETHICONE 5; MAGNESIUM CHLORIDE; POTASSIUM CHLORIDE; ZINC CHLORIDE; LYSINE; HYALURONATE SODIUM; PHENOXYETHANOL; HEXYLENE GLYCOL; CAPRYLYL GLYCOL; POTASSIUM SORBATE; MICA; FERRIC OXIDE RED

Drug Facts

Active Ingredients

Titanium Dioxide 4.50%

Zinc Oxide 3.00%

Purpose

Sunscreen

Sunscreen

Use

- Helps prevent sunburn
- If used as directed with other sun protection measures (see directions), decreases the risk of skin cancer and early skin aging caused by the sun.

Warnings

For external use only

Do not use on damaged or broken skin.

Stop use and ask doctor if rash occurs.

When using this product keep out of eyes. Rinse with water to remove.

Keep out of reach of children. If swollowed, get medical help or contact a Poison Control Center right away.

Directions

- Apply liberally 15 minutes before sun exposure
- Use a water resistant sunscreen if swimming or sweating
- Reapply at least every 2 hours
- Children under 6 months: ask a doctor
- Sun Protection Measures. Spending time in the sun increases risk of skin cancer and early aging. To decrease this risk regularly use a sunscreen with a Broad Spectrum SPF value of 15 or higer and other sun protection measures including
- Limit time in the sun especially from 10:00 a.m. - 2:00 p.m.
- Wear long sleeved shirts, pants, hats and sunglasses

Inactive Ingredients

Water (Aqua), Cyclopentaslloxane, Octyldodecyl Neopentanoate, Butylene Glycol, Glycerin, Polyglyceryl-4 Isostearate, Dimethicone Crosspolymer, PEG/PPG 18/18 Dimethicone, Silica, Dimethicone, Cetyl PEG/PPG-10/1 Dimethicone, Stearic Acid, Aluminum Hydroxide, Sodium Dehydroacetate, Phytantriol, Hexyl Laurate, Triethoxycaprylylsilane, Nylon-12, Carbomer, Polysorbate 20, Palmitoyl Oligopeptide, Palmitoyl Tetrapeptide-7, Sodium Chloride, Tocopherol, Tetrahexyldecyl Ascorbate, Nylon-12 Fluorescent Brightener 230 Salt, Polyvinylalconol Crosspolymer, Magnesium Chloride, Potassium Chloride, Zinc Chloride, Lysine, Sodium Hyaluronate, Phenoxyethanol, Hexylene Glycol, Caprylyl Glycol, Potassium Sorbate, May Contain: Mica, Titanium Dioxide (CI 77891), Iron Oxides (CI 77491, CI 77492, CI 77499)

Other Information

- Protect this product from excessive heat and direct sun.

Distibuted by Mallygirl LLC

P.O. Box 42727

Baltimore, MD 21284-2727

Product made in USA

Principal Display Panel

mally

Face Defender BB

cream foundation

BROAD SPECTRUM SPF 15

Tube

Box